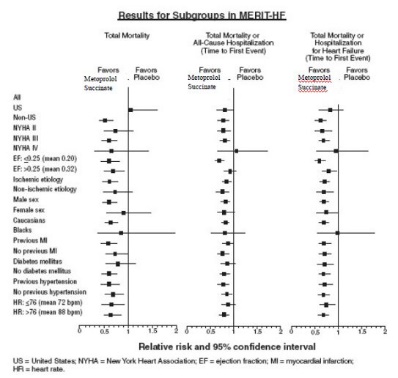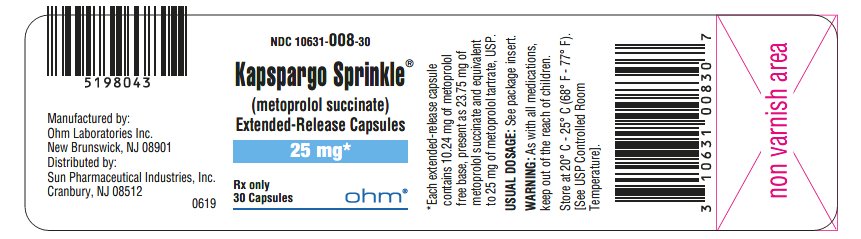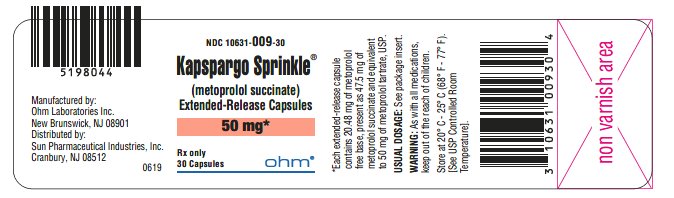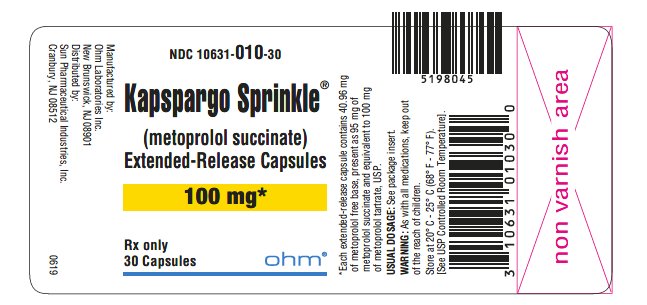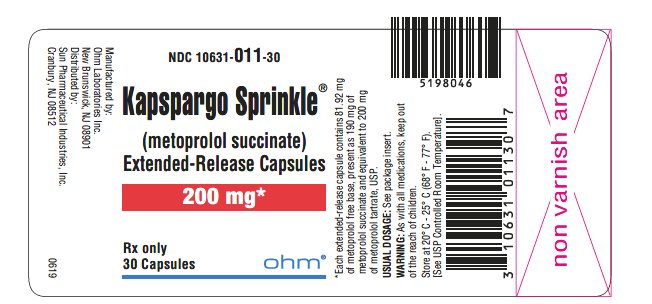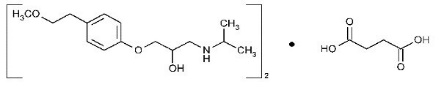 DRUG LABEL: KAPSPARGO
NDC: 10631-008 | Form: CAPSULE, EXTENDED RELEASE
Manufacturer: Sun Pharmaceutical Industries, Inc.
Category: prescription | Type: HUMAN PRESCRIPTION DRUG LABEL
Date: 20230412

ACTIVE INGREDIENTS: METOPROLOL SUCCINATE 25 mg/1 1
INACTIVE INGREDIENTS: HYPROMELLOSE 2910 (5 MPA.S); ETHYLCELLULOSE (20 MPA.S); POLYETHYLENE GLYCOL 400; POLYETHYLENE GLYCOL 6000; SUCROSE; STARCH, CORN; TALC; TRIETHYL CITRATE; FERRIC OXIDE YELLOW; FERROSOFERRIC OXIDE; GELATIN, UNSPECIFIED; POTASSIUM HYDROXIDE; SHELLAC; TITANIUM DIOXIDE; PROPYLENE GLYCOL

HIGHLIGHTS OF PRESCRIBING INFORMATION

These highlights do not include all the information needed to use KAPSPARGO SPRINKLE safely and effectively. See full prescribing information for KAPSPARGO SPRINKLE.
KAPSPARGO SPRINKLE® (metoprolol succinate) capsules extended-release, for Oral Use
Initial U.S. Approval: 1992

1 INDICATIONS AND USAGE

KAPSPARGO Sprinkle is a beta1-adrenergic blocker indicated for the treatment of:
• Hypertension, to lower blood pressure. Lowering blood pressure reduces the risk of fatal and non-fatal cardiovascular events, primarily strokes and myocardial infarctions. (1.1)
• Angina Pectoris. (1.2)
• Heart Failure, to reduce the risk of cardiovascular mortality and heart-failure hospitalizations in patients with heart failure. (1.3)

2 DOSAGE AND ADMINISTRATION

- Adult Hypertension: Usual initial dosage is 25 to 100 mg once daily. Titrate weekly (or longer) to optimal blood pressure. (2.1)
- Pediatric Hypertension 6 years of age and older: The recommended starting dose is 1 mg/kg, once daily and titrate to response. Do not exceed a maximum initial dose of 50 mg once daily. (2.1)
- Angina Pectoris: Usual initial dosage is 100 mg once daily. Titrate weekly based on clinical response. (2.2)
- Heart Failure: The recommended starting dose is 25 mg once daily doubled every two weeks to the highest dose tolerated or up to 200 mg. (2.3)

3 DOSAGE FORMS AND STRENGTHS

• KAPSPARGO Sprinkle extended-release capsules: 25 mg, 50 mg, 100 mg, and 200 mg. (3)

4 CONTRAINDICATIONS

• Known hypersensitivity to product components. (4)
• Severe bradycardia: Greater than first degree heart block, or sick sinus syndrome without a pacemaker. (4)
• Cardiogenic shock or decompensated heart failure. (4)

5 WARNINGS AND PRECAUTIONS

• Abrupt cessation may exacerbate myocardial ischemia. (5.1)
• Heart Failure: Worsening cardiac failure may occur. (5.2)
• Bronchospastic Disease: Avoid beta blockers. (5.3)
• Concomitant use of glycosides, clonidine, diltiazem and verapamil with beta-blockers can increase the risk of bradycardia. (5.4)
• Pheochromocytoma: Initiate therapy with an alpha blocker. (5.5)
• Major Surgery: Avoid initiation of high-dose extended-release metoprolol in patients undergoing non-cardiac surgery. Do not routinely withdraw chronic beta-blocker therapy prior to surgery. (5.6, 6.1)
• Hypoglycemia: May increase risk for hypoglycemia and mask early warning signs. (5.7)
• Thyrotoxicosis: Abrupt withdrawal in patients with thyrotoxicosis might precipitate a thyroid storm. (5.8)
• Peripheral Vascular Disease: Can aggravate symptoms of arterial insufficiency. (5.9)
• Patients may be unresponsive to the usual doses of epinephrine used to treat allergic reaction. (5.10)

6 ADVERSE REACTIONS

• Most common adverse reactions: tiredness, dizziness, depression, shortness of breath, bradycardia, hypotension, diarrhea, pruritus, rash. (6.1)
To report SUSPECTED ADVERSE REACTIONS, contact Sun Pharmaceutical Industries, Inc. at 1-800-406-7984 or FDA at 1-800-FDA-1088 or www.fda.gov/medwatch.

7 DRUG INTERACTIONS

• Catecholamine-depleting drugs may have an additive effect when given with beta-blocking agents. (7.1)
• CYP2D6 Inhibitors are likely to increase metoprolol concentration. (7.2)
• Beta-blockers including metoprolol, may exacerbate the rebound hypertension that can follow the withdrawal of clonidine. (7.3)

8 USE IN SPECIFIC POPULATIONS

- Hepatic Impairment: Consider initiating metoprolol succinate therapy at low doses and gradually increase dosage to optimize therapy, while monitoring closely for adverse events. (8.6)

FULL PRESCRIBING INFORMATION

1 INDICATIONS AND USAGE

1.1 Hypertension

KAPSPARGO Sprinkle is indicated for the treatment of hypertension, to lower blood pressure. Lowering blood pressure lowers the risk of fatal and non-fatal cardiovascular events, primarily strokes and myocardial infarctions. These benefits have been seen in controlled trials of antihypertensive drugs from a wide variety of pharmacologic classes including metoprolol.

Control of high blood pressure should be part of comprehensive cardiovascular risk management, including, as appropriate, lipid control, diabetes management, antithrombotic therapy, smoking cessation, exercise, and limited sodium intake. Many patients will require more than 1 drug to achieve blood pressure goals. For specific advice on goals and management, see published guidelines, such as those of the National High Blood Pressure Education Program's Joint National Committee on Prevention, Detection, Evaluation, and Treatment of High Blood Pressure (JNC).

Numerous antihypertensive drugs, from a variety of pharmacologic classes and with different mechanisms of action, have been shown in randomized controlled trials to reduce cardiovascular morbidity and mortality, and it can be concluded that it is blood pressure reduction, and not some other pharmacologic property of the drugs, that is largely responsible for those benefits. The largest and most consistent cardiovascular outcome benefit has been a reduction in the risk of stroke, but reductions in myocardial infarction and cardiovascular mortality also have been seen regularly.

Elevated systolic or diastolic pressure causes increased cardiovascular risk, and the absolute risk increase per mmHg is greater at higher blood pressures, so that even modest reductions of severe hypertension can provide substantial benefit. Relative risk reduction from blood pressure reduction is similar across populations with varying absolute risk, so the absolute benefit is greater in patients who are at higher risk independent of their hypertension (for example, patients with diabetes or hyperlipidemia), and such patients would be expected to benefit from more aggressive treatment to a lower blood pressure goal.

Some antihypertensive drugs have smaller blood pressure effects (as monotherapy) in black patients, and many antihypertensive drugs have additional approved indications and effects (e.g., on angina, heart failure, or diabetic kidney disease). These considerations may guide selection of therapy.

KAPSPARGO Sprinkle may be administered with other antihypertensive agents.

1.2 Angina Pectoris

KAPSPARGO Sprinkle is indicated in the long-term treatment of angina pectoris, to reduce angina attacks and to improve exercise tolerance.

1.3 Heart Failure

KAPSPARGO Sprinkle is indicated to reduce the risk of cardiovascular mortality and heart-failure hospitalization in patients with heart failure.

2 DOSAGE AND ADMINISTRATION

2.1 Hypertension

Adults: The usual initial dosage is 25 mg to 100 mg once daily in a single dose. Adjust dosage at weekly (or longer) intervals until optimum blood pressure reduction is achieved. Dosages above 400 mg per day have not been studied.

Pediatric Hypertensive Patients 6 Years of age or older: The recommended starting dose of KAPSPARGO Sprinkle is 1 mg/kg once daily, the maximum initial dose should not exceed 50 mg once daily. Adjust dosage according to blood pressure response. Doses above 2 mg/kg (or in excess of 200 mg) once daily have not been studied in pediatric patients [see Clinical Pharmacology (12.3)].

KAPSPARGO Sprinkle has not been studied in pediatric patients less than 6 years of age [see Use in Specific Populations (8.4)].

2.2 Angina Pectoris

Individualize the dosage of KAPSPARGO Sprinkle. The usual initial dosage is 100 mg once daily, given in a single dose. Gradually increase the dosage at weekly intervals until optimum clinical response has been obtained or there is a pronounced slowing of the heart rate. Dosages above 400 mg per day have not been studied. If treatment is to be discontinued, reduce the dosage gradually over a period of 1 to 2 weeks [see Warnings and Precautions (5)].

2.3 Heart Failure

Prior to initiation of KAPSPARGO Sprinkle, stabilize the dose of other heart failure drug therapy and ensure that the patient is not fluid overloaded. The recommended starting dose of KAPSPARGO Sprinkle is 25 mg once daily for two weeks. KAPSPARGO Sprinkle is not suitable for initial therapy in patients who are expected to require a starting dose less than 25 mg daily. Dosage must be individualized and closely monitored during up-titration. Double the dose every two weeks to the highest dosage level tolerated by the patient or up to 200 mg of KAPSPARGO Sprinkle. If a patient experiences symptomatic bradycardia, reduce the dose of KAPSPARGO Sprinkle. If transient worsening of heart failure occurs, consider treating with increased doses of diuretics, lowering the dose of KAPSPARGO Sprinkle or temporarily discontinuing it. The dose of KAPSPARGO Sprinkle should not be increased until symptoms of worsening heart failure have been stabilized. Initial difficulty with titration should not preclude later attempts to introduce KAPSPARGO Sprinkle.

For patients who are taking metoprolol succinate extended-release tablets at a dose of 25 mg to 200 mg once daily, substitute KAPSPARGO Sprinkle for metoprolol succinate extended-release tablets, using the same total daily dose of metoprolol succinate.

2.4 Administration

KAPSPARGO Sprinkle should be swallowed whole. For patients unable to swallow an intact capsule, alternative administration options are available. Directions for use with soft food (applesauce, pudding, or yogurt) For patients with swallowing difficulty, KAPSPARGO Sprinkle can be opened and contents can be sprinkled over soft food. The contents of the capsules should be swallowed along with a small amount (teaspoonful) of soft food (such as applesauce, pudding, or yogurt). The drug/food mixture should be swallowed within 60 minutes and not stored for future use. Nasogastric tube administration Open and add contents of capsule to an all plastic oral tip syringe and add 15 mL of water. Gently shake the syringe for approximately 10 seconds. Promptly deliver through a 12 French or larger nasogastric tube. Ensure no pellets are left in the syringe. Rinse with additional water if needed.

3 DOSAGE FORMS AND STRENGTHS

25 mg capsule: Light yellow opaque cap and white opaque body both imprinted with 'RL14' in black ink containing white to off-white pellets.

50 mg capsule: Dark yellow opaque cap and white opaque body both imprinted with 'RL15' in black ink containing white to off-white pellets.

100 mg capsule: White opaque cap and white opaque body both imprinted with 'RL16' in black ink containing white to off-white pellets.

200 mg capsule: Yellow opaque cap and yellow opaque body both imprinted with 'RL17' in black ink containing white to off-white pellets.

4 CONTRAINDICATIONS

Metoprolol succinate is contraindicated in severe bradycardia, second- or third-degree heart block, cardiogenic shock, decompensated heart failure, sick sinus syndrome (unless a permanent pacemaker is in place), and in patients who are hypersensitive to any component of this product.

5 WARNINGS AND PRECAUTIONS

5.1 Abrupt Cessation of Therapy

Following abrupt cessation of therapy with certain beta-blocking agents, exacerbations of angina pectoris and, in some cases, myocardial infarction have occurred. When discontinuing chronically administered metoprolol succinate, particularly in patients with ischemic heart disease, gradually reduce the dosage over a period of 1 to 2 weeks and monitor the patient. If angina markedly worsens or acute coronary ischemia develops, promptly reinstate metoprolol succinate, and take measures appropriate for the management of unstable angina. Warn patients not to interrupt therapy without their physician's advice. Because coronary artery disease is common and may be unrecognized, avoid abruptly discontinuing metoprolol succinate in patients treated only for hypertension.

5.2 Heart Failure

Worsening cardiac failure may occur during up-titration of metoprolol succinate. If such symptoms occur, increase diuretics and restore clinical stability before advancing the dose of metoprolol succinate [see Dosage and Administration (2)]. It may be necessary to lower the dose of metoprolol succinate or temporarily discontinue it. Such episodes do not preclude subsequent successful titration of metoprolol succinate.

5.3 Bronchospastic Disease

Patients with bronchospastic diseases should, in general, not receive beta-blockers. Because of its relative beta1-cardio-selectivity, however, metoprolol succinate may be used in patients with bronchospastic disease who do not respond to, or cannot tolerate, other antihypertensive treatment. Because beta1-selectivity is not absolute, use the lowest possible dose of metoprolol succinate. Bronchodilators, including beta2-agonists, should be readily available or administered concomitantly [see Dosage and Administration (2)].

5.4 Bradycardia

Bradycardia, including sinus pause, heart block, and cardiac arrest have occurred with the use of metoprolol succinate. Patients with first-degree atrioventricular block, sinus node dysfunction, conduction disorders (including Wolff-Parkinson-White) or on concomitant drugs that cause bradycardia [see Drug Interactions (7.3)], may be at increased risk. Monitor heart rate in patients receiving metoprolol succinate. If severe bradycardia develops, reduce or stop metoprolol succinate.

5.5 Pheochromocytoma

If metoprolol succinate is used in the setting of pheochromocytoma, it should be given in combination with an alpha-blocker, and only after the alpha-blocker has been initiated. Administration of beta-blockers alone in the setting of pheochromocytoma has been associated with a paradoxical increase in blood pressure due to the attenuation of beta-mediated vasodilatation in skeletal muscle.

5.6 Major Surgery

Avoid initiation of a high-dose regimen of extended-release metoprolol in patients undergoing non-cardiac surgery, since such use in patients with cardiovascular risk factors has been associated with bradycardia, hypotension, stroke, and death.

Chronically administered beta-blocking therapy should not be routinely withdrawn prior to major surgery; however, the impaired ability of the heart to respond to reflex adrenergic stimuli may augment the risks of general anesthesia and surgical procedures.

5.7 Hypoglycemia

Beta-blockers may prevent early warning signs of hypoglycemia, such as tachycardia, and increase the risk for severe or prolonged hypoglycemia at any time during treatment, especially in patients with diabetes mellitus or children and patients who are fasting (i.e., surgery, not eating regularly, or are vomiting). If severe hypoglycemia occurs, patients should be instructed to seek emergency treatment.

5.8 Thyrotoxicosis

Beta-adrenergic blockade may mask certain clinical signs of hyperthyroidism, such as tachycardia. Abrupt withdrawal of beta-blockade may precipitate a thyroid storm.

5.9 Peripheral Vascular Disease

Beta-blockers can precipitate or aggravate symptoms of arterial insufficiency in patients with peripheral vascular disease.

5.10 Anaphylactic Reaction

While taking beta-blockers, patients with a history of severe anaphylactic reactions to a variety of allergens may be more reactive to repeated challenge and may be unresponsive to the usual doses of epinephrine used to treat an allergic reaction.

6 ADVERSE REACTIONS

The following adverse reactions are described elsewhere in labeling:

- Worsening angina or myocardial infarction [see Warnings and Precautions (5)]
- Worsening heart failure [see Warnings and Precautions (5)]
- Worsening AV block [see Contraindications (4)]

6.1 Clinical Trials Experience

Because clinical trials are conducted under widely varying conditions, adverse reaction rates observed in the clinical trials of a drug cannot be directly compared to rates in the clinical trials of another drug and may not reflect the rates observed in practice. The adverse reaction information from clinical trials does, however, provide a basis for identifying the adverse events that appear to be related to drug use and for approximating rates.

Hypertension and Angina: Most adverse reactions have been mild and transient. The most common (> 2%) adverse reactions are tiredness, dizziness, depression, diarrhea, shortness of breath, bradycardia, and rash.

Heart Failure: In the MERIT-HF study comparing metoprolol succinate in daily doses up to 200 mg (mean dose 159 mg once-daily; n = 1990) to placebo (n = 2001), 10.3% of metoprolol succinate patients discontinued for adverse events vs. 12.2% of placebo patients.

The table below lists adverse reactions in the MERIT-HF study that occurred at an incidence of ≥ 1% in the metoprolol succinate group and greater than placebo by more than 0.5%, regardless of the assessment of causality.

Adverse Reactions Occurring in the MERIT-HF Study at an Incidence ≥ 1% in the Metoprolol Succinate Group and Greater Than Placebo by More Than 0.5%

 | Metoprolol Succinate; n = 1990 % of patients | Placebo; n = 2001 % of patients
Dizziness/vertigo | 1.8 | 1
Bradycardia | 1.5 | 0.4

Post-operative Adverse Events: In a randomized, double-blind, placebo-controlled trial of 8351 patients with or at risk for atherosclerotic disease undergoing non-vascular surgery and who were not taking beta–blocker therapy, metoprolol succinate 100 mg was started 2 to 4 hours prior to surgery then continued for 30 days at 200 mg per day. Metoprolol succinate use was associated with a higher incidence of bradycardia (6.6% vs. 2.4%; HR, 2.74; 95% CI 2.19, 3.43), hypotension (15% vs. 9.7%; HR 1.55; 95% CI 1.37, 1.74), stroke (1.0% vs. 0.5%; HR 2.17; 95% CI 1.26, 3.74) and death (3.1% vs. 2.3%; HR 1.33; 95% CI 1.03, 1.74) compared to placebo.

6.2 Post-Marketing Experience

The following adverse reactions have been identified during post-approval use of extended-release metoprolol or immediate-release metoprolol. Because these reactions are reported voluntarily from a population of uncertain size, it is not always possible to reliably estimate their frequency or establish a causal relationship to drug exposure.

Cardiovascular: Cold extremities, arterial insufficiency (usually of the Raynaud type), palpitations, peripheral edema, syncope, chest pain and hypotension.

Respiratory: Wheezing (bronchospasm), dyspnea.

Central Nervous System: Confusion, short-term memory loss, headache, somnolence, nightmares, insomnia, anxiety/nervousness, hallucinations, paresthesia.

Gastrointestinal: Nausea, dry mouth, constipation, flatulence, heartburn, hepatitis, vomiting.

Hypersensitive Reactions: Pruritus.

Miscellaneous: Musculoskeletal pain, arthralgia, blurred vision, decreased libido, male impotence, tinnitus, reversible alopecia, agranulocytosis, dry eyes, worsening of psoriasis, Peyronie's disease, sweating, photosensitivity, taste disturbance.

Potential Adverse Reactions: In addition, there are adverse reactions not listed above that have been reported with other beta-adrenergic blocking agents and should be considered potential adverse reactions to metoprolol succinate.

Central Nervous System: Reversible mental depression progressing to catatonia; an acute reversible syndrome characterized by disorientation for time and place, short-term memory loss, emotional lability, clouded sensorium, and decreased performance on neuropsychometrics.

Hematologic: Agranulocytosis, nonthrombocytopenic purpura, thrombocytopenic purpura.

Hypersensitive Reactions: Laryngospasm, respiratory distress.

7 DRUG INTERACTIONS

7.1 Catecholamine Depleting Drugs

Catecholamine depleting drugs (e.g., reserpine, monoamine oxidase (MAO) inhibitors) may have an additive effect when given with beta-blocking agents. Observe patients treated with metoprolol succinate plus a catecholamine depletor for evidence of hypotension or marked bradycardia, which may produce vertigo, syncope, or postural hypotension.

7.2 CYP2D6 Inhibitors

Drugs that are strong inhibitors of CYP2D6 such as quinidine, fluoxetine, paroxetine, and propafenone were shown to double metoprolol concentrations. While there is no information about moderate or weak inhibitors, these too are likely to increase metoprolol concentration. Increases in plasma concentration decrease the cardioselectivity of metoprolol [see Clinical Pharmacology (12.3)]. Monitor patients closely, when the combination cannot be avoided.

7.3 Digitalis, Clonidine, and Calcium Channel Blockers

Digitalis glycosides, clonidine, diltiazem, and verapamil slow atrioventricular conduction and decrease heart rate. Concomitant use with beta-blockers can increase the risk of bradycardia.

If clonidine and a beta-blocker, such as metoprolol are co-administered, withdraw the beta-blocker several days before the gradual withdrawal of clonidine because beta-blockers may exacerbate the rebound hypertension that can follow the withdrawal of clonidine. If replacing clonidine by beta-blocker therapy, delay the introduction of beta-blockers for several days after clonidine administration has stopped.

7.4 Alcohol

Metoprolol succinate is released faster from KAPSPARGO Sprinkle in the presence of alcohol. This may increase the risk for adverse events associated with KAPSPARGO Sprinkle. Avoid alcohol consumption when taking KAPSPARGO Sprinkle [see Clinical Pharmacology (12.3)].

8 USE IN SPECIFIC POPULATIONS

8.1 Pregnancy

Risk Summary
Untreated hypertension and heart failure during pregnancy can lead to adverse outcomes for the mother and the fetus (see Clinical Considerations). Available data from published observational studies have not demonstrated a drug-associated risk of major birth defects, miscarriage, or adverse maternal or fetal outcomes with metoprolol use during pregnancy. However, there are inconsistent reports of intrauterine growth restriction, preterm birth, and perinatal mortality with maternal use of beta blockers, including metoprolol, during pregnancy (see Data). In animal reproduction studies, metoprolol has been shown to increase post-implantation loss and decrease neonatal survival in rats at oral dosages of 500 mg/kg/day, approximately 24 times the daily dose of 200 mg in a 60-kg patient on a mg/m^2 basis.
The estimated background risk of major birth defects and miscarriage for the indicated population is unknown. All pregnancies have a background risk of birth defect, loss, or other adverse outcomes. In the U.S. general population, the estimated background risk of major birth defects and miscarriage in clinically recognized pregnancies is 2 to 4% and 15 to 20%, respectively.
Clinical consideration
Disease-associated maternal and/or embryo/fetal risk
Hypertension in pregnancy increases the maternal risk for pre-eclampsia, gestational diabetes, premature delivery, and delivery complications (e.g., need for cesarean section, and post-partum hemorrhage).
Hypertension increases the fetal risk for intrauterine growth restriction and intrauterine death. Pregnant women with hypertension should be carefully monitored and managed accordingly.
Stroke volume and heart rate increase during pregnancy, increasing cardiac output, especially during the first trimester. There is a risk for preterm birth with pregnant women with chronic heart failure in 3rd trimester of pregnancy.
Fetal/Neonatal adverse reactions
Metoprolol crosses the placenta. Neonates born to mothers who are receiving metoprolol during pregnancy, may be at risk for hypotension, hypoglycemia, bradycardia, and respiratory depression. Observe neonates and manage accordingly.
Data
Human Data
Data from published observational studies did not demonstrate an association of major congenital malformations and use of metoprolol in pregnancy. The published literature has reported inconsistent findings of intrauterine growth retardation, preterm birth, and perinatal mortality with maternal use of metoprolol during pregnancy; however, these studies have methodological limitations hindering interpretation. Methodological limitations include retrospective design, concomitant use of other medications, and other unadjusted confounders that may account for the study findings including the underlying disease in the mother. These observational studies cannot definitely establish or exclude any drug-associated risk during pregnancy.
Animal Data
Metoprolol has been shown to increase post-implantation loss and decrease neonatal survival in rats at oral dosages of 500 mg/kg/day, i.e., 24 times, on a mg/m2 basis, the daily dose of 200 mg in a 60-kg patient.
No fetal abnormalities were observed when pregnant rats received metoprolol orally up to a dose of 200 mg/kg/day, i.e., 10 times, the daily dose of 200 mg in a 60-kg patient.

8.2 Lactation

Risk Summary

Limited available data from published literature report that metoprolol is present in human milk. The estimated daily infant dose of metoprolol received from breastmilk ranges from 0.05 mg to less than 1 mg. The estimated relative infant dosage was 0.5% to 2% of the mother's weight-adjusted dosage (see Data). No adverse reactions of metoprolol on the breastfed infant have been identified. There is no information regarding the effects of metoprolol on milk production.

Clinical consideration

Monitoring for adverse reactions

Monitor the breastfed infant for bradycardia and other symptoms of beta-blockade such as listlessness (hypoglycemia).

Data

Based on published case reports, the estimated infant daily dose of metoprolol received from breast milk range from 0.05 mg to less than 1 mg. The estimated relative infant dosage was 0.5% to 2% of the mother’s weight- adjusted dosage.

In two women who were taking unspecified amount of metoprolol, milk samples were taken after one dose of metoprolol. The estimated amount of metoprolol and alpha-hydroxy metoprolol in breast milk is reported to be less than 2% of the mother's weight-adjusted dosage.

In a small study, breast milk was collected every 2 to 3 hours over one dosage interval, in three mothers (at least 3 months postpartum) who took metoprolol of unspecified amount. The average amount of metoprolol present in breast milk was 71.5 mcg/day (range 17.0 to 158.7). The average relative infant dosage was 0.5% of the mother's weight-adjusted dosage.

8.3 Females and Males of Reproductive Potential

Risk Summary

Based on the published literature, beta-blockers (including metoprolol) may cause erectile dysfunction and inhibit sperm motility.

No evidence of impaired fertility due to metoprolol was observed in rats [see Nonclinical Toxicology (13.1)].

8.4 Pediatric Use

One hundred forty-four hypertensive pediatric patients aged 6 to 16 years were randomized to placebo or to one of three dose levels of metoprolol succinate (0.2, 1 or 2 mg/kg once daily) and followed for 4 weeks. The study did not meet its primary endpoint (dose response for reduction in SBP). Some pre-specified secondary endpoints demonstrated effectiveness including:

•Dose-response for reduction in DBP,

•1 mg/kg vs. placebo for change in SBP, and

•2 mg/kg vs. placebo for change in SBP and DBP.

The mean placebo corrected reductions in SBP ranged from 3 to 6 mmHg, and DBP from 1 to 5 mmHg. Mean reduction in heart rate ranged from 5 to 7 bpm but considerably greater reductions were seen in some individuals [see Dosage and Administration (2.1)].

No clinically relevant differences in the adverse event profile were observed for pediatric patients aged 6 to 16 years as compared with adult patients.

Safety and effectiveness of metoprolol succinate have not been established in patients < 6 years of age.

8.5 Geriatric Use

Clinical studies of metoprolol succinate in hypertension did not include sufficient numbers of subjects aged 65 and over to determine whether they respond differently from younger subjects. Other reported clinical experience in hypertensive patients has not identified differences in responses between elderly and younger patients.

Of the 1,990 patients with heart failure randomized to metoprolol succinate in the MERIT-HF trial, 50% (990) were 65 years of age and older and 12% (238) were 75 years of age and older. There were no notable differences in efficacy or the rate of adverse reactions between older and younger patients.

In general, use a low initial starting dose in elderly patients given their greater frequency of decreased hepatic, renal, or cardiac function, and of concomitant disease or other drug therapy.

8.6 Hepatic Impairment

No studies have been performed with metoprolol succinate in patients with hepatic impairment. Because metoprolol succinate is metabolized by the liver, metoprolol blood levels are likely to increase substantially with poor hepatic function. Therefore, initiate therapy at doses lower than those recommended for a given indication; and increase doses gradually in patients with impaired hepatic function.

8.7 Renal Impairment

The systemic availability and half-life of metoprolol in patients with renal failure do not differ to a clinically significant degree from those in normal subjects. No reduction in dosage is needed in patients with chronic renal failure [see Clinical Pharmacology (12.3)].

10 OVERDOSAGE

Signs and Symptoms - Overdosage of metoprolol succinate may lead to severe bradycardia, hypotension, and cardiogenic shock. Clinical presentation can also include: atrioventricular block, heart failure, bronchospasm, hypoxia, impairment of consciousness/coma, nausea and vomiting.

Treatment – Consider treating the patient with intensive care. Patients with myocardial infarction or heart failure may be prone to significant hemodynamic instability. Beta-blocker overdose may result in significant resistance to resuscitation with adrenergic agents, including beta-agonists. On the basis of the pharmacologic actions of metoprolol, employ the following measures.

Hemodialysis is unlikely to make a useful contribution to metoprolol elimination [see Clinical Pharmacology (12.3)].

Bradycardia: Evaluate the need for atropine, adrenergic-stimulating drugs, or pacemaker to treat bradycardia and conduction disorders.

Hypotension: Treat underlying bradycardia. Consider intravenous vasopressor infusion, such as dopamine or norepinephrine.

Heart failure and shock: May be treated when appropriate with suitable volume expansion, injection of glucagon (if necessary, followed by an intravenous infusion of glucagon), intravenous administration of adrenergic drugs such as dobutamine, with α1 receptor agonistic drugs added in presence of vasodilation.

Bronchospasm: Can usually be reversed by bronchodilators.

11 DESCRIPTION

Metoprolol succinate, is a beta1-selective (cardioselective) adrenoceptor blocking agent, for oral administration, available as extended-release capsules. Metoprolol succinate extended-release capsules have been formulated to provide a controlled and predictable release of metoprolol for once-daily administration. The extended-release capsules comprise a multiple unit system containing metoprolol succinate in a multitude of controlled release pellets. Each pellet acts as a separate drug delivery unit and is designed to deliver metoprolol continuously over the dosage interval. The extended-release capsules contain 10.24 mg, 20.48 mg, 40.96 mg, and 81.92 mg of metoprolol free base, present as 23.75 mg, 47.5 mg, 95 mg, and 190 mg of metoprolol succinate and are equivalent to 25 mg, 50 mg, 100 mg, and 200 mg of metoprolol tartrate, USP, respectively. Its chemical name is (±)-1-(Isopropylamino)-3-[p-(2-methoxyethyl)phenoxy]-2-propanol succinate (2:1) (salt). Its structural formula is:

Metoprolol succinate, USP is a white to off-white powder with a molecular weight of 652.82. It is freely soluble in water, soluble in methanol, sparingly soluble in alcohol, slightly soluble in isopropyl alcohol. Inactive ingredients: ethyl cellulose, hypromellose, polyethylene glycol 400, polyethylene glycol 6000, sugar spheres (corn starch and sucrose), talc and triethyl citrate. The capsule shell and imprinting ink has the following composition: ferric oxide yellow (25 mg, 50 mg and 200 mg), ferrosoferric oxide, gelatin, potassium hydroxide, propylene glycol, shellac and titanium dioxide.

12 CLINICAL PHARMACOLOGY

12.1 Mechanism of Action

Metoprolol is a beta1-selective (cardioselective) adrenergic receptor blocking agent. This preferential effect is not absolute, however, and at higher plasma concentrations, metoprolol also inhibits beta2-adrenoreceptors, chiefly located in the bronchial and vascular musculature.

Metoprolol has no intrinsic sympathomimetic activity, and membrane-stabilizing activity is detectable only at plasma concentrations much greater than required for beta-blockade. Animal and human experiments indicate that metoprolol slows the sinus rate and decreases AV nodal conduction.

The relative beta1-selectivity of metoprolol has been confirmed by the following: (1) In normal subjects, metoprolol is unable to reverse the beta2-mediated vasodilating effects of epinephrine. This contrasts with the effect of nonselective beta-blockers, which completely reverse the vasodilating effects of epinephrine. (2) In asthmatic patients, metoprolol reduces FEV1 and FVC significantly less than a nonselective beta-blocker, propranolol, at equivalent beta1-receptor blocking doses.

Hypertension: The mechanism of the antihypertensive effects of beta-blocking agents has not been elucidated. However, several possible mechanisms have been proposed: (1) competitive antagonism of catecholamines at peripheral (especially cardiac) adrenergic neuron sites, leading to decreased cardiac output; (2) a central effect leading to reduced sympathetic outflow to the periphery; and (3) suppression of renin activity.

Angina Pectoris: By blocking catecholamine-induced increases in heart rate, in velocity and extent of myocardial contraction, and in blood pressure, metoprolol reduces the oxygen requirements of the heart at any given level of effort, thus making it useful in the long-term management of angina pectoris.

Heart Failure: The precise mechanism for the beneficial effects of beta-blockers in heart failure has not been elucidated.

12.2 Pharmacodynamics

Clinical pharmacology studies have confirmed the beta-blocking activity of metoprolol in man, as shown by (1) reduction in heart rate and cardiac output at rest and upon exercise, (2) reduction of systolic blood pressure upon exercise, (3) inhibition of isoproterenol-induced tachycardia, and (4) reduction of reflex orthostatic tachycardia.

The relationship between plasma metoprolol levels and reduction in exercise heart rate is independent of the pharmaceutical formulation. Beta1-blocking effects in the range of 30 to 80% of the maximal effect (approximately 8 to 23% reduction in exercise heart rate) correspond to metoprolol plasma concentrations from 30 to 540 nmol/L. The relative beta1-selectivity of metoprolol diminishes and blockade of beta2-adrenoceptors increases at plasma concentration above 300 nmol/L.

In five controlled studies in normal healthy subjects, extended-release metoprolol succinate administered once a day, and immediate-release metoprolol administered once to four times a day, provided comparable total beta1-blockade over 24 hours (area under the beta1-blockade versus time curve) in the dose range 100 to 400 mg. In another controlled study, 50 mg once daily for each product, extended-release metoprolol succinate produced significantly higher total beta1-blockade over 24 hours than immediate-release metoprolol. For extended-release metoprolol succinate, the percent reduction in exercise heart rate was relatively stable throughout the entire dosage interval and the level of beta1-blockade increased with increasing doses from 50 to 300 mg daily.

A controlled cross-over study in heart failure patients compared the plasma concentrations and beta1-blocking effects of 50 mg immediate-release metoprolol administered t.i.d., and 100 mg and 200 mg extended-release metoprolol succinate once daily. Extended-release metoprolol succinate 200 mg once daily produced a larger effect on suppression of exercise-induced and Holter-monitored heart rate over 24 hours compared to 50 mg t.i.d. of immediate-release metoprolol.

In other studies, treatment with metoprolol succinate produced an improvement in left ventricular ejection fraction. Metoprolol succinate was also shown to delay the increase in left ventricular end-systolic and end-diastolic volumes after 6 months of treatment.

Although beta-adrenergic receptor blockade is useful in the treatment of angina, hypertension, and heart failure there are situations in which sympathetic stimulation is vital. In patients with severely damaged hearts, adequate ventricular function may depend on sympathetic drive. In the presence of AV block, beta-blockade may prevent the necessary facilitating effect of sympathetic activity on conduction. Beta2-adrenergic blockade results in passive bronchial constriction by interfering with endogenous adrenergic bronchodilator activity in patients subject to bronchospasm and may also interfere with exogenous bronchodilators in such patients.

12.3 Pharmacokinetics

Absorption

The peak plasma levels following once-daily administration of extended release metoprolol succinate are reduced by 50 to 75% on average compared to a corresponding dose of immediate-release metoprolol tartrate, both when administered once daily or in divided doses. At steady state the average bioavailability of metoprolol following administration of metoprolol succinate, across the dosage range of 50 to 400 mg once daily, was reduced by 25% relative to the corresponding single or divided doses of immediate-release metoprolol tartrate. The bioavailability of metoprolol shows a dose-related, although not directly proportional, increase with dose. The exposure (Cmax and AUC) of metoprolol succinate extended-release capsule are similar to that of TOPROL-XL® tablet.

Absorption

Plasma levels following oral administration of metoprolol tablet approximate 50% of levels following intravenous administration, indicating about 50% first-pass metabolism. Peak plasma concentration of metoprolol is attained at 10 hours following administration of metoprolol succinate extended-release capsule.

Effect of food

Compared to fasted state administration, high-fat, high-calorie meal (54.3% fat, 15.6% proteins and 30.1% carbohydrates) did not have a significant effect on the absorption of KAPSPARGO Sprinkle.

KAPSPARGO Sprinkle (metoprolol succinate 200 mg) administered under fasting conditions to healthy adults by sprinkling the entire contents on one-tablespoon (15 mL) of applesauce did not significantly affect Tmax, Cmax, and AUC of metoprolol.

Distribution

About 12% of the drug is bound to human serum albumin.

Metoprolol crosses the blood-brain barrier and has been reported in the CSF in a concentration 78% of the simultaneous plasma concentration.

Elimination

Elimination is mainly by biotransformation in the liver, and the plasma half-life ranges from approximately 3 to 7 hours.

Metabolism

Metoprolol is a racemic mixture of R- and S- enantiomers, and is primarily metabolized by CYP2D6. When administered orally, it exhibits stereoselective metabolism that is dependent on oxidation phenotype.

Excretion

Less than 5% of an oral dose of metoprolol is recovered unchanged in the urine; the rest is excreted by the kidneys as metabolites that appear to have no beta-blocking activity.

Following intravenous administration of metoprolol, the urinary recovery of unchanged drug is approximately 10%.

Specific Populations

Patients with Renal Impairment
The systemic availability and half-life of metoprolol in patients with renal failure do not differ to a clinically significant degree from those in normal subjects.

Pediatric Patients

The pharmacokinetic profile of metoprolol succinate was studied in 120 pediatric hypertensive patients (6 to 17 years of age) receiving doses ranging from 12.5 to 200 mg once daily. The pharmacokinetics of metoprolol were similar to those described previously in adults. Age, gender, race, and ideal body weight had no significant effects on metoprolol pharmacokinetics. Metoprolol apparent oral clearance (CL/F) increased linearly with body weight. Metoprolol pharmacokinetics have not been investigated in patients < 6 years of age.

Body Weight, Age, and Race
Metoprolol apparent oral clearance (CL/F) increased linearly with body weight. Age, gender, and race had no significant effects on metoprolol pharmacokinetics.

Drug Interactions

CYP2D6

Metoprolol is metabolized predominantly by CYP2D6. In healthy subjects with CYP2D6 extensive metabolizer phenotype, coadministration of quinidine 100 mg, a potent CYP2D6 inhibitor, and immediate-release metoprolol 200 mg tripled the concentration of S-metoprolol and doubled the metoprolol elimination half-life. In four patients with cardiovascular disease, coadministration of propafenone 150 mg t.i.d. with immediate-release metoprolol 50 mg t.i.d. resulted in steady-state concentration of metoprolol 2- to 5-fold what is seen with metoprolol alone. Extensive metabolizers who concomitantly use CYP2D6 inhibiting drugs will have increased (several-fold) metoprolol blood levels, decreasing metoprolol's cardioselectivity [see Drug Interactions (7.2)].

Alcohol

An in vitro dissolution study was conducted to evaluate the impact of alcohol (5, 10, 20 and 40%), on the extended-release characteristics of KAPSPARGO Sprinkle. The in vitro study showed that about 89% of the total metoprolol succinate dose was released at 2 hour at the highest alcohol level (40%), and about 17% of total drug was released at 2 hour with 5% alcohol. Alcohol causes a rapid release of metoprolol succinate from KAPSPARGO Sprinkle that may increase the risk for above events associated with KAPSPARGO Sprinkle. Consumption of alcohol is not recommended when taking KAPSPARGO Sprinkle 25 mg, 50 mg, 100 mg and 200 mg.

13 NONCLINICAL TOXICOLOGY

13.1 Carcinogenesis, Mutagenesis, Impairment of Fertility

Long-term studies in animals have been conducted to evaluate the carcinogenic potential of metoprolol tartrate. In 2-year studies in rats at three oral dosage levels of up to 800 mg/kg/day (41 times, on a mg/m^2 basis, the daily dose of 200 mg for a 60 kg patient), there was no increase in the development of spontaneously occurring benign or malignant neoplasms of any type. The only histologic changes that appeared to be drug related were an increased incidence of generally mild focal accumulation of foamy macrophages in pulmonary alveoli and a slight increase in biliary hyperplasia. In a 21-month study in Swiss albino mice at three oral dosage levels of up to 750 mg/kg/day (18 times, on a mg/m^2 basis, the daily dose of 200 mg for a 60-kg patient), benign lung tumors (small adenomas) occurred more frequently in female mice receiving the highest dose than in untreated control animals. There was no increase in malignant or total (benign plus malignant) lung tumors, nor in the overall incidence of tumors or malignant tumors. This 21-month study was repeated in CD-1 mice, and no statistically or biologically significant differences were observed between treated and control mice of either sex for any type of tumor.

All genotoxicity tests performed on metoprolol tartrate (a dominant lethal study in mice, chromosome studies in somatic cells, a Salmonella/mammalian-microsome mutagenicity test, and a nucleus anomaly test in somatic interphase nuclei) and metoprolol succinate (a Salmonella/mammalian-microsome mutagenicity test) were negative.

No evidence of impaired fertility due to metoprolol tartrate was observed in a study performed in rats at doses up to 22 times, on a mg/m^2 basis, the daily dose of 200 mg in a 60-kg patient.

14 CLINICAL STUDIES

14.1 Hypertension

In a double-blind study, 1092 patients with mild-to-moderate hypertension were randomized to once daily metoprolol succinate (25, 100, or 400 mg), PLENDIL® (felodipine extended-release tablets), the combination, or placebo. After 9 weeks, metoprolol succinate alone decreased sitting blood pressure by 6 – 8 mmHg /4 - 7 mmHg (placebo-corrected change from baseline) at 24 hours post-dose. The combination of metoprolol succinate with PLENDIL® has greater effects on blood pressure.

In controlled clinical studies, an immediate-release dosage form of metoprolol was an effective antihypertensive agent when used alone or as concomitant therapy with thiazide-type diuretics at dosages of 100 to 450 mg daily. Metoprolol succinate, in dosages of 100 to 400 mg once daily, produces similar β1-blockade as conventional metoprolol tablets administered two to four times daily. In addition, metoprolol succinate administered at a dose of 50 mg once daily lowered blood pressure 24-hours post-dosing in placebo-controlled studies. In controlled, comparative, clinical studies, immediate-release metoprolol appeared comparable as an antihypertensive agent to propranolol, methyldopa, and thiazide-type diuretics, and affected both supine and standing blood pressure. Because of variable plasma levels attained with a given dose and lack of a consistent relationship of antihypertensive activity to drug plasma concentration, selection of proper dosage requires individual titration.

14.2 Angina Pectoris

In controlled clinical trials, an immediate-release formulation of metoprolol has been shown to be an effective antianginal agent, reducing the number of angina attacks and increasing exercise tolerance. The dosage used in these studies ranged from 100 to 400 mg daily. Metoprolol succinate, in dosages of 100 to 400 mg once daily, has been shown to possess beta- blockade similar to conventional metoprolol tablets administered two to four times daily.

14.3 Heart Failure

MERIT-HF was a randomized, double-blind study in which 3991 patients with ejection fraction ≤0.40 and NYHA Class II-IV heart failure attributable to ischemia, hypertension, or cardiomyopathy were randomized 1:1 to metoprolol or placebo. The protocol excluded patients with contraindications to beta-blocker use, those expected to undergo heart surgery, and those within 28 days of myocardial infarction or unstable angina. The primary endpoints of the trial were (1) all-cause mortality plus all-cause hospitalization (time to first event) and (2) all-cause mortality. Patients were stabilized on optimal concomitant therapy for heart failure, including diuretics, ACE inhibitors, cardiac glycosides, and nitrates. At randomization, 41% of patients were NYHA Class II; 55% NYHA Class III; 65% of patients had heart failure attributed to ischemic heart disease; 44% had a history of hypertension; 25% had diabetes mellitus; 48% had a history of myocardial infarction. Among patients in the trial, 90% were on diuretics, 89% were on ACE inhibitors, 64% were on digitalis, 27% were on a lipid-lowering agent, 37% were on an oral anticoagulant, and the mean ejection fraction was 0.28. The mean duration of follow-up was one year. At the end of the study, the mean daily dose of metoprolol succinate was 159 mg.

The trial was terminated early for a statistically significant reduction in all-cause mortality (34%, nominal p= 0.00009). The risk of all-cause mortality plus all-cause hospitalization was reduced by 19% (p= 0.00012). The trial also showed improvements in heart failure-related mortality and heart failure-related hospitalizations, and NYHA functional class.

The table below shows the principal results for the overall study population. The figure below illustrates principal results for a wide variety of subgroup comparisons, including US vs. non-US populations (the latter of which was not pre-specified). The combined endpoints of all-cause mortality plus all-cause hospitalization and of mortality plus heart failure hospitalization showed consistent effects in the overall study population and the subgroups. Nonetheless, subgroup analyses can be difficult to interpret and it is not known whether these represent true differences or chance effects.

Clinical Endpoints in the MERIT-HF Study

Clinical Endpoint | Number of Patients |  | Relative Risk; (95% Cl) | Risk Reduction With Metoprolol Succinate | Nominal P-; value
 | Placebo; n=2001 | Metoprolol Succinate; n=1990
All-cause mortality plus all-caused hospitalization^1 | 767 | 641 | 0.81; (0.73 to 0.90) | 19% | 0.00012
All-cause mortality | 217 | 145 | 0.66; (0.53 to 0.81) | 34% | 0.00009
All-cause mortality plus heart failure hospitalization^1 | 439 | 311 | 0.69; (0.60 to 0.80) | 31% | 0.0000008
Cardiovascular mortality | 203 | 128 | 0.62; (0.50to 0.78) | 38% | 0.000022
Sudden death | 132 | 79 | 0.59; (0.45 to 0.78) | 41% | 0.0002
Death due to worsening heart; failure | 58 | 30 | 0.51; (0.33 to 0.79) | 49% | 0.0023
Hospitalizations due to worsening heart failure^2 | 451 | 317 | N/A | N/A | 0.0000076
Cardiovascular hospitalization^2 | 773 | 649 | N/A | N/A | 0.00028

^1. Time to first event

^2.Comparison of treatment groups examines the number of hospitalizations (Wilcoxon test); relative risk and risk reduction are not applicable.

16 HOW SUPPLIED/STORAGE AND HANDLING

Each extended-release capsule contains 10.24 mg, 20.48 mg, 40.96 mg, and 81.92 mg of metoprolol free base, present as 23.75 mg, 47.5 mg, 95 mg, and 190 mg of metoprolol succinate and equivalent to 25 mg, 50 mg, 100 mg, and 200 mg of metoprolol tartrate, USP respectively and are supplied as follows:
25 mg capsule: Light yellow opaque cap and white opaque body both imprinted with ‘RL14’ in black ink containing white to off-white pellets.
NDC 10631-008-30 Bottle of 30
50 mg capsule: Dark yellow opaque cap and white opaque body both imprinted with ‘RL15’ in black ink containing white to off-white pellets.
NDC 10631-009-30 Bottles of 30
100 mg capsule: White opaque cap and white opaque body both imprinted with ‘RL16’ in black ink containing white to off-white pellets.
NDC 10631-010-30 Bottles of 30
200 mg capsule: Yellow opaque cap and yellow opaque body both imprinted with ‘RL17’ in black ink containing white to off-white pellets.
NDC 10631-011-30 Bottles of 30
Store at 20° C - 25° C (68° F - 77° F). [See USP Controlled Room Temperature].

17 PATIENT COUNSELING INFORMATION

Advise patients to take KAPSPARGO Sprinkle regularly and continuously, as directed, preferably with or immediately following meals. If a dose is missed, the patient should take only the next scheduled dose (without doubling it). Patients should not interrupt or discontinue KAPSPARGO Sprinkle without consulting the physician.
Advise patients (1) to avoid operating automobiles and machinery or engaging in other tasks requiring alertness until the patient’s response to therapy with KAPSPARGO Sprinkle has been determined; (2) to contact the physician if any difficulty in breathing occurs; (3) to inform the physician or dentist before any type of surgery that he or she is taking KAPSPARGO Sprinkle.
Heart failure patients should be advised to consult their physician if they experience signs or symptoms of worsening heart failure such as weight gain or increasing shortness of breath.
Risk of hypoglycemia
Inform patients or caregivers that there is a risk of hypoglycemia when KAPSPARGO Sprinkle is given to patients who are fasting or who are vomiting. Instruct patients or caregivers how to monitor for signs of hypoglycemia [see Warnings and Precautions (5.7)].

KAPSPARGO Sprinkle is a trademark of Sun Pharmaceutical Industries Limited. All other trademarks are property of their respective owners.

Manufactured by:
Ohm Laboratories Inc.
New Brunswick, NJ 08901

Distributed by:
Sun Pharmaceutical Industries, Inc.
Cranbury, NJ 08512
FDA-09

PACKAGE/LABEL PRINCIPAL DISPLAY PANEL - 25 mg

NDC 10631-008-30

Kapspargo Sprinkle®

(metoprolol succinate)

Extended-Release Capsules

25 mg*

Rx only

30 Capsules

ohm®

PACKAGE/LABEL PRINCIPAL DISPLAY PANEL - 50 mg

NDC 10631-009-30

Kapspargo Sprinkle®

(metoprolol succinate)

Extended-Release Capsules

50 mg*

Rx only

30 Capsules

ohm®

PACKAGE/LABEL PRINCIPAL DISPLAY PANEL - 100 mg

NDC 10631-010-30

Kapspargo Sprinkle®

(metoprolol succinate)

Extended-Release Capsules

100 mg*

Rx only

30 Capsules

ohm®

PACKAGE/LABEL PRINCIPAL DISPLAY PANEL - 200 mg

NDC 10631-011-30

Kapspargo Sprinkle®

(metoprolol succinate)

Extended-Release Capsules

200 mg*

Rx only

30 Capsules

ohm®